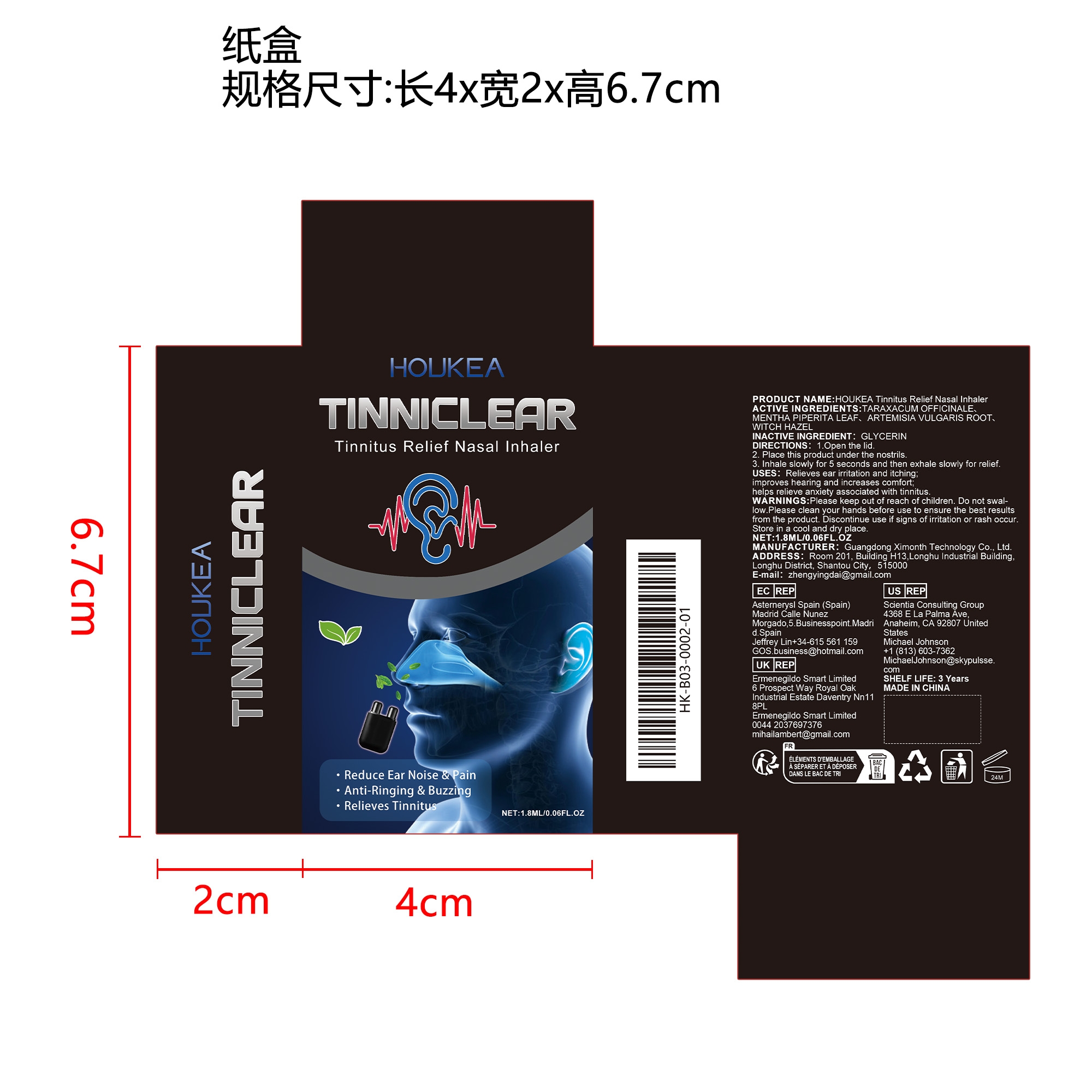 DRUG LABEL: HOUKEA Tinnitus Relief Nasal Inhaler
NDC: 84660-097 | Form: CREAM
Manufacturer: Guangdong Ximonth Technology Co., Ltd.
Category: otc | Type: HUMAN OTC DRUG LABEL
Date: 20241031

ACTIVE INGREDIENTS: WITCH HAZEL 0.4 mg/1.8 mg; MENTHA PIPERITA LEAF 0.2 mg/1.8 mg; TARAXACUM OFFICINALE 0.2 mg/1.8 mg; ARTEMISIA VULGARIS ROOT 0.4 mg/1.8 mg
INACTIVE INGREDIENTS: GLYCERIN 0.6 mg/1.8 mg

Active Ingredient(s)

TARAXACUM OFFICINALE、MENTHA PIPERITA LEAF、ARTEMISIA VULGARIS ROOT、WITCH HAZEL

Purpose

Relieves ear irritation and itching; improves hearing and increases comfort; helps relieve anxiety associated with tinnitus.

Use

1.Open the lid.
2. Place this product under the nostrils.
3. Inhale slowly for 5 seconds and then exhale slowly for relief.

Warnings

Please keep out of reach of children.Do not swallow.Please clean your hands before use to ensure the best results from the product.Discontinue use if signs of irritation or rash occur.Store in a cool and dry place.

Do not use

Discontinue use if signs of irritation or rash occur.

Stop Use

Discontinue use if signs of irritation or rash occur.

KEEP OUT OF REACH OF CHILDREN

Please keep out of reach of children. Do not swallow.

STORAGE AND HANDLING

Store in a cool and dry place.

INACTIVE INGREDIENT

GLYCERIN